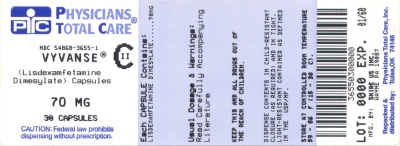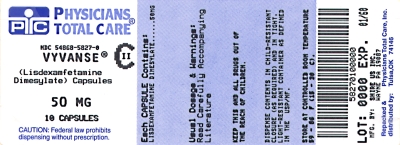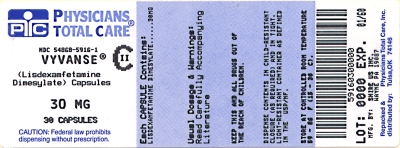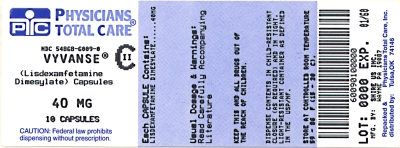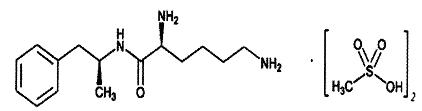 DRUG LABEL: Vyvanse
NDC: 54868-5916 | Form: CAPSULE
Manufacturer: Physicians Total Care, Inc.
Category: prescription | Type: HUMAN PRESCRIPTION DRUG LABEL
Date: 20120113
DEA Schedule: CII

ACTIVE INGREDIENTS: LISDEXAMFETAMINE DIMESYLATE 30 mg/1 1
INACTIVE INGREDIENTS: CELLULOSE, MICROCRYSTALLINE; CROSCARMELLOSE SODIUM; MAGNESIUM STEARATE; GELATIN; TITANIUM DIOXIDE; D&C RED NO. 28; D&C YELLOW NO. 10; FD&C BLUE NO. 1; FD&C GREEN NO. 3; FD&C RED NO. 40; FERROSOFERRIC OXIDE; FERRIC OXIDE YELLOW; FD&C RED NO. 3; FD&C YELLOW NO. 6

HIGHLIGHTS OF PRESCRIBING INFORMATION

These highlights do not include all the information needed to use Vyvanse safely and effectively. See full prescribing information for Vyvanse.
Vyvanse® (lisdexamfetamine dimesylate) Capsules, CII
Initial U.S. Approval: 2007

WARNING: POTENTIAL FOR ABUSE

See full prescribing information for complete boxed warning

- Amphetamines have a high potential for abuse; prolonged administration may lead to dependence (9)
- Misuse of amphetamines may cause sudden death and serious cardiovascular adverse events

RECENT MAJOR CHANGES

Indications and Usage, Adolescents (1.1) 11/2010

Dosage and Administration, Adolescents (2) 11/2010

Warnings and Precautions, Long Term Suppression of Growth (5.6) 11/2010

1 INDICATIONS AND USAGE

Vyvanse, a prodrug of the CNS stimulant dextroamphetamine, is indicated for the treatment of Attention Deficit Hyperactivity Disorder (ADHD). (1)

- Children: Efficacy was established in two trials in 6-12 year olds with ADHD. (14)
- Adolescents: Efficacy was established in one trial in 13-17 year olds with ADHD (14)
- Adults: Efficacy was established in two trials in adults with ADHD. (14)

2 DOSAGE AND ADMINISTRATION

- Recommended dose: Adults and pediatric patients ages (6-17); 30 mg once daily in the morning (2)
- Maximum dose: 70 mg once daily in the morning (2)

3 DOSAGE FORM AND STRENGTHS

- Capsules: 20 mg, 30 mg, 40 mg, 50 mg, 60 mg, 70 mg (3)

4 CONTRAINDICATIONS

- Advanced arteriosclerosis (4)
- Symptomatic cardiovascular disease (4)
- Moderate to severe hypertension (4)
- Hyperthyroidism (4)
- Known hypersensitivity or idiosyncrasy to sympathomimetic amines (4)
- Glaucoma (4)
- Agitated states (4)
- History of drug abuse (4)
- During or within 14 days following the administration of monoamine oxidase inhibitors (MAOI) (4, 7.3)

5 WARNINGS AND PRECAUTIONS

- Serious Cardiovascular Events: Sudden death has been reported in association with CNS stimulant treatment at usual doses in children and adolescents with structural cardiac abnormalities or other serious heart problems. Sudden death, stroke, and myocardial infarction have been reported in adults taking stimulant drugs at usual doses for ADHD. Stimulant products generally should not be used in patients with known structural cardiac abnormalities, cardiomyopathy, serious heart rhythm abnormalities, coronary artery disease, or other serious heart problems. (5.1)
- Increase in Blood Pressure: Monitor blood pressure and pulse at appropriate intervals in patients taking Vyvanse. Use with caution in patients for whom blood pressure increases may be problematic. (5.1)
- Psychiatric Adverse Events: Use of stimulants may cause treatment-emergent psychotic or manic symptoms in patients with no prior history, or exacerbation of symptoms in patients with pre-existing psychosis. Clinical evaluation for bipolar disorder is recommended prior to stimulant use. Monitor for aggressive behavior. (5.2)
- Seizures: may lower the convulsive threshold, and in the presence of seizures, should be discontinued. (5.3)
- Visual Disturbance: difficulties with accommodation and blurring of vision have been reported with stimulant treatment. (5.4)
- Tics: may exacerbate tics. Clinical evaluation for tics and Tourette's syndrome is recommended prior to stimulant administration. (5.5)
- Long-Term Suppression of Growth: monitor height and weight at appropriate intervals in pediatric patients taking Vyvanse. (5.6)

6 ADVERSE REACTIONS

- Children ages 6 to 12: Most common adverse reactions (incidence ≥5% and at a rate at least twice placebo) were decreased appetite, dizziness, dry mouth, irritability, insomnia, upper abdominal pain, nausea, vomiting, and decreased weight. (6.1)
- Adolescents ages 13 to 17: Most common adverse reactions (incidence ≥5% and at a rate at least twice placebo) were decreased appetite, insomnia, and decreased weight. (6.1)
- Adults: Most common adverse reactions (incidence ≥5% and at a rate at least twice placebo) were upper abdominal pain, diarrhea, nausea, fatigue, feeling jittery, irritability, anorexia, decreased appetite, headaches, anxiety, and insomnia. (6.1)

To report SUSPECTED ADVERSE REACTIONS, contact Shire US Inc. at 1-800-828-2088 or FDA at 1-800-FDA-1088 or www.fda.gov/medwatch

7 DRUG INTERACTIONS

- Urinary acidifying agents may reduce blood levels of amphetamine. (7.2)
- Urinary alkalinizing agents may increase blood levels of amphetamine. (7.3)
- MAOI antidepressants are contraindicated. (4; 7.3)
- The effects of adrenergic blockers, antihistamines, antihypertensives, phenobarbital, and phenytoin may be reduced by amphetamines. (7.4)
- The effects of tricyclic antidepressants, meperidine, phenobarbital and phenytoin may be potentiated by amphetamines. (7.5)
- Norepinephrine may potentiate the effects of amphetamines. (7.7)

8 USE IN SPECIFIC POPULATIONS

- Pregnancy: Use only if the potential benefit justifies the potential risk to the fetus. Based on animal data, may cause fetal harm. (8.1)
- Nursing Mothers: should refrain from breastfeeding. (8.3)
- Pediatric Use: has not been studied in children under 6 years of age. (8.4)
- Geriatric Use: has not been studied in geriatric patients. (8.5)

FULL PRESCRIBING INFORMATION

WARNING: POTENTIAL FOR ABUSE

AMPHETAMINES HAVE A HIGH POTENTIAL FOR ABUSE. ADMINISTRATION OF AMPHETAMINES FOR PROLONGED PERIODS OF TIME MAY LEAD TO DRUG DEPENDENCE. PARTICULAR ATTENTION SHOULD BE PAID TO THE POSSIBILITY OF SUBJECTS OBTAINING AMPHETAMINES FOR NON-THERAPEUTIC USE OR DISTRIBUTION TO OTHERS AND THE DRUGS SHOULD BE PRESCRIBED OR DISPENSED SPARINGLY.

MISUSE OF AMPHETAMINES MAY CAUSE SUDDEN DEATH AND SERIOUS CARDIOVASCULAR ADVERSE EVENTS.

1 INDICATIONS AND USAGE

1.1 Attention Deficit Hyperactivity Disorder

Vyvanse® is indicated for the treatment of Attention Deficit Hyperactivity Disorder (ADHD).

The efficacy of Vyvanse in the treatment of ADHD was established on the basis of two controlled trials in children aged 6 to 12, one controlled trial in adolescents aged 13 to 17, and two controlled trials in adults who met DSM-IV-TR® criteria for ADHD [see CLINICAL STUDIES (14)].

A diagnosis of Attention Deficit Hyperactivity Disorder (ADHD; DSM-IV®) implies the presence of hyperactive-impulsive and/or inattentive symptoms that cause impairment and were present before the age of 7 years. The symptoms must cause clinically significant impairment, e.g. in social, academic, or occupational functioning, and be present in two or more settings, e.g. school (or work) and at home. The symptoms must not be better accounted for by another mental disorder. For the Inattentive Type, at least 6 of the following symptoms must have persisted for at least 6 months: lack of attention to details/careless mistakes; lack of sustained attention; poor listener; failure to follow through on tasks; poor organization; avoids tasks requiring sustained mental effort; loses things; easily distracted; forgetful. For the Hyperactive-Impulsive Type, at least 6 of the following symptoms (or adult equivalent symptoms) must have persisted for at least 6 months: fidgeting/squirming; leaving seat; inappropriate running/climbing; difficulty with quiet activities; "on the go"; excessive talking; blurting answers; can't wait turn; intrusive. The Combined Type requires both inattentive and hyperactive-impulsive criteria to be met.

Special Diagnostic Considerations

Specific etiology of this syndrome is unknown, and there is no single diagnostic test. Adequate diagnosis requires the use not only of medical but also of special psychological, educational, and social resources. Learning may or may not be impaired. The diagnosis must be based upon a complete history and evaluation of the patient and not solely on the presence of the required number of DSM-IV characteristics.

Need for Comprehensive Treatment Program

Vyvanse is indicated as an integral part of a total treatment program for ADHD that may include other measures (psychological, educational, social) for patients with this syndrome. Drug treatment may not be indicated for all patients with this syndrome. Stimulants are not intended for use in patients who exhibit symptoms secondary to environmental factors and/or other primary psychiatric disorders, including psychosis. Appropriate educational/vocational placement is essential and psychosocial intervention is often helpful. When remedial measures alone are insufficient, the decision to prescribe stimulant medication will depend upon the physician's assessment of the chronicity and severity of the patient's symptoms and on the level of functional impairment.

Long-Term Use

The effectiveness of Vyvanse for long-term use, i.e., for more than 4 weeks, has not been systematically evaluated in controlled trials. Therefore, the physician who elects to use Vyvanse for extended periods should periodically re-evaluate the long-term usefulness of the drug for the individual patient.

2 DOSAGE AND ADMINISTRATION

Dosage should be individualized according to the therapeutic needs and response of the patient. Vyvanse should be administered at the lowest effective dosage.

In patients who are either starting treatment for the first time or switching from another medication, 30 mg once daily in the morning is the recommended dose. If the decision is made in the judgment of the clinician to increase the dose beyond 30 mg/day, daily dosage may be adjusted in increments of 10 mg or 20 mg at approximately weekly intervals. The maximum recommended dose is 70 mg/day; doses greater than 70 mg/day of Vyvanse have not been studied. Vyvanse has not been studied in children under 6 years of age.

Vyvanse should be taken in the morning. Afternoon doses should be avoided because of the potential for insomnia.

Vyvanse may be taken with or without food.

Vyvanse capsules may be taken whole, or the capsule may be opened and the entire contents dissolved in a glass of water. The solution should be consumed immediately and should not be stored. The dose of a single capsule should not be divided. The contents of the entire capsule should be taken, and patients should not take anything less than one capsule per day.

Where possible, drug administration should be interrupted occasionally to determine if there is a recurrence of behavioral symptoms sufficient to require continued treatment.

3 DOSAGE FORM AND STRENGTHS

Vyvanse capsules 20 mg: ivory body/ivory cap (imprinted with NRP104 or S489 and 20 mg)

Vyvanse capsules 30 mg: white body/orange cap (imprinted with NRP104 or S489 and 30 mg)

Vyvanse capsules 40 mg: white body/blue green cap (imprinted with NRP104 or S489 and 40 mg)

Vyvanse capsules 50 mg: white body/blue cap (imprinted with NRP104 or S489 and 50 mg)

Vyvanse capsules 60 mg: aqua blue body/aqua blue cap (imprinted with NRP104 or S489 and 60 mg)

Vyvanse capsules 70 mg: blue body/orange cap (imprinted with NRP104 or S489 and 70 mg)

4 CONTRAINDICATIONS

- Advanced arteriosclerosis, symptomatic cardiovascular disease, moderate to severe hypertension, hyperthyroidism, known hypersensitivity or idiosyncratic reaction to sympathomimetic amines, glaucoma
- Agitated states
- Patients with a history of drug abuse
- During or within 14 days following the administration of monoamine oxidase inhibitors (hypertensive crises may result) [See Drug Interactions (7.3)]

5 WARNINGS AND PRECAUTIONS

5.1 Serious Cardiovascular Events

Sudden Death and Pre-existing Structural Cardiac Abnormalities or Other Serious Heart Problems

Children and Adolescents

Sudden death has been reported in association with CNS stimulant treatment at usual doses in children and adolescents with structural cardiac abnormalities or other serious heart problems. Although some serious heart problems alone carry an increased risk of sudden death, stimulant products generally should not be used in children or adolescents with known serious structural cardiac abnormalities, cardiomyopathy, serious heart rhythm abnormalities, or other serious cardiac problems that may place them at increased vulnerability to the sympathomimetic effects of a stimulant drug [see CONTRAINDICATIONS (4)].

Adults

Sudden death, stroke, and myocardial infarction have been reported in adults taking stimulant drugs at usual doses for ADHD. Although the role of stimulants in these adult cases is unknown, adults have a greater likelihood than children of having serious structural cardiac abnormalities, cardiomyopathy, serious heart rhythm abnormalities, coronary artery disease, or other serious cardiac problems. Adults with such abnormalities should also generally not be treated with stimulant drugs [see CONTRAINDICATIONS (4)].

Hypertension and Other Cardiovascular Conditions

Stimulant medications cause a modest increase in average blood pressure (about 2-4 mm Hg) and average heart rate (about 3-6 bpm) and individuals may have larger increases. While the mean changes alone would not be expected to have short-term consequences, all patients should be monitored for larger changes in heart rate and blood pressure. Caution is indicated in treating patients whose underlying medical conditions might be compromised by increases in blood pressure or heart rate, e.g. those with pre-existing hypertension, heart failure, recent myocardial infarction, or ventricular arrhythmia [see CONTRAINDICATIONS (4)].

Assessing Cardiovascular Status in Patients Being Treated with Stimulant Medications

Children, adolescents, or adults who are being considered for treatment with stimulant medications should have a careful history (including assessment for a family history of sudden death or ventricular arrhythmia) and physical exam to assess for the presence of cardiac disease, and should receive further cardiac evaluation if findings suggest such disease (e.g. electrocardiogram and echocardiogram). Patients who develop symptoms such as exertional chest pain, unexplained syncope, or other symptoms suggestive of cardiac disease during stimulant treatment should undergo a prompt cardiac evaluation.

5.2 Psychiatric Adverse Events

Pre-existing Psychosis

Administration of stimulants may exacerbate symptoms of behavior disturbance and thought disorder in patients with a pre-existing psychotic disorder.

Bipolar Illness

Particular care should be taken in using stimulants to treat ADHD in patients with comorbid bipolar disorder because of concern for possible induction of a mixed/manic episode in such patients. Prior to initiating treatment with a stimulant, patients with comorbid depressive symptoms should be adequately screened to determine if they are at risk for bipolar disorder. Such screening should include a detailed psychiatric history, including a family history of suicide, bipolar disorder, and depression.

Emergence of New Psychotic or Manic Symptoms

Treatment-emergent psychotic or manic symptoms, e.g. hallucinations, delusional thinking, or mania in children and adolescents without a prior history of psychotic illness or mania, can be caused by stimulants at usual doses. If such symptoms occur, consideration should be given to a possible causal role of the stimulant, and discontinuation of treatment may be appropriate. In a pooled analysis of multiple short-term, placebo-controlled studies, such symptoms occurred in about 0.1% (4 patients with events out of 3482 exposed to methylphenidate or amphetamine for several weeks at usual doses) of stimulant-treated patients compared to 0 in placebo-treated patients.

Aggression

Aggressive behavior or hostility is often observed in children and adolescents with ADHD, and has been reported in clinical trials and the postmarketing experience of some medications indicated for the treatment of ADHD. Although there is no systematic evidence that stimulants cause aggressive behavior or hostility, patients beginning treatment of ADHD should be monitored for the appearance of, or worsening of, aggressive behavior or hostility.

5.3 Seizures

There is some clinical evidence that stimulants may lower the convulsive threshold in patients with prior history of seizures, in patients with prior EEG abnormalities in absence of seizures, and, very rarely, in patients without a history of seizures and no prior EEG evidence of seizures. In the presence of seizures, the drug should be discontinued.

5.4 Visual Disturbance

Difficulties with accommodation and blurring of vision have been reported with stimulant treatment.

5.5 Tics

Amphetamines have been reported to exacerbate motor and phonic tics and Tourette's syndrome. Therefore, clinical evaluation for tics and Tourette's syndrome should precede use of stimulant medications.

5.6 Long-Term Suppression of Growth

In a controlled trial of Vyvanse in children ages 6 to 12 years, mean weight loss from baseline after 4 weeks of therapy was -0.9, -1.9, and -2.5 lbs., respectively, for patients receiving 30 mg, 50 mg, and 70 mg of Vyvanse, compared to a 1 lb weight gain for patients receiving placebo. Higher doses were associated with greater weight loss with 4 weeks of treatment. Careful follow-up for weight in children ages 6 to 12 years who received Vyvanse over 12 months suggests that consistently medicated children (i.e. treatment for 7 days per week throughout the year) have a slowing in growth rate, measured by body weight as demonstrated by an age- and sex-normalized mean change from baseline in percentile, of -13.4 over 1 year (average percentiles at baseline and 12 months were 60.6 and 47.2, respectively). In a 4-week controlled trial of Vyvanse in adolescents ages 13 to 17 years, mean weight loss from baseline to endpoint was -2.7, -4.3, and -4.8 lbs., respectively, for patients receiving 30 mg, 50 mg, and 70 mg of Vyvanse, compared to a 2.0 lb weight gain for patients receiving placebo.

Careful follow-up of weight and height in children ages 7 to 10 years who were randomized to either methylphenidate or non-medication treatment groups over 14 months, as well as in naturalistic subgroups of newly methylphenidate-treated and non-medication treated children over 36 months (to the ages of 10 to 13 years), suggests that consistently medicated children (i.e. treatment for 7 days per week throughout the year) have a temporary slowing in growth rate (on average, a total of about 2 cm less growth in height and 2.7 kg less growth in weight over 3 years), without evidence of growth rebound during this period of development. In a controlled trial of amphetamine (d- to l-enantiomer ratio of 3:1) in adolescents, mean weight change from baseline within the initial 4 weeks of therapy was -1.1 lbs. and -2.8 lbs., respectively, for patients receiving 10 mg and 20 mg of amphetamine. Higher doses were associated with greater weight loss within the initial 4 weeks of treatment.

Therefore, growth should be monitored during treatment with stimulants, and patients who are not growing or gaining weight as expected may need to have their treatment interrupted.

5.7 Prescribing and Dispensing

The least amount of amphetamine feasible should be prescribed or dispensed at one time in order to minimize the possibility of overdosage. Vyvanse should be used with caution in patients who use other sympathomimetic drugs.

6 ADVERSE REACTIONS

6.1 Clinical Studies Experience

The premarketing development program for Vyvanse included exposures in a total of 995 participants in clinical trials (348 pediatric patients aged 6 to 12 years, 233 adolescent patients aged 13 to 17 years, 358 adult patients and 56 healthy adult subjects). Of these, 348 pediatric (aged 6 to 12) patients were evaluated in two controlled clinical studies (one parallel-group and one crossover), one open-label extension study, and one single-dose clinical pharmacology study, 233 adolescent (aged 13 to 17) patients were evaluated in one controlled clinical study, and 358 adult patients were evaluated in one controlled clinical study and one open-label extension study. The information included in this section is based on data from the 4-week parallel-group controlled clinical studies in pediatric and adult patients with ADHD. Adverse reactions were assessed by collecting adverse events, results of physical examinations, vital signs, weights, laboratory analyses, and ECGs.

Adverse reactions during exposure were obtained primarily by general inquiry and recorded by clinical investigators using terminology of their own choosing. Consequently, it is not possible to provide a meaningful estimate of the proportion of individuals experiencing adverse reactions without first grouping similar types of reactions into a smaller number of standardized reactions categories. In the tables and listings that follow, MedDRA terminology has been used to classify reported adverse reactions.

The stated frequencies of adverse reactions represent the proportion of individuals who experienced a treatment-emergent adverse reaction of the type listed at least once.

Adverse Reactions Associated with Discontinuation of Treatment in Clinical Trials

In the controlled pediatric (aged 6 to 12) trial, 9% (20/218) of Vyvanse-treated patients discontinued due to adverse reactions compared to 1% (1/72) who received placebo. The most frequent adverse events leading to discontinuation and considered to be drug-related (i.e. leading to discontinuation in at least 1% of Vyvanse-treated patients and at a rate at least twice that of placebo) were ECG voltage criteria for ventricular hypertrophy, tic, vomiting, psychomotor hyperactivity, insomnia, and rash (2/218 each; 1%).

In the controlled adolescent (aged 13 to 17) trial, 4% (10/233) of Vyvanse-treated patients discontinued due to adverse events compared to 1% (1/77) who received placebo. The most frequent adverse reactions leading to discontinuation and considered to be drug-related were irritability (3/233; 1%), decreased appetite (2/233; 1%), and insomnia (2/233; 1%).

In the controlled adult trial, 6% (21/358) of Vyvanse-treated patients discontinued due to adverse events compared to 2% (1/62) who received placebo. The most frequent adverse events leading to discontinuation and considered to be drug-related (i.e. leading to discontinuation in at least 1% of Vyvanse-treated patients and at a rate at least twice that of placebo) were insomnia (8/358; 2%), tachycardia (3/358; 1%), irritability (2/358; 1%), hypertension (4/358; 1%), headache (2/358; 1%), anxiety (2/358; 1%), and dyspnea (3/358; 1%).

Adverse Reactions Occurring at an Incidence of 2% or More Among Vyvanse Treated Patients in Clinical Trials

Adverse reactions reported in the controlled trials in pediatric (aged 6 to 17 years) and adult patients treated with Vyvanse or placebo are presented in Tables 1, 2, and 3 below. The prescriber should be aware that these figures cannot be used to predict the incidence of adverse reactions in the course of usual medical practice where patient characteristics and other factors differ from those which prevailed in the clinical trials. Similarly, the cited frequencies cannot be compared with figures obtained from other clinical investigations involving different treatment uses and investigators. The cited figures, however, do provide the prescribing physician with some basis for estimating the relative contribution of drug and non-drug factors to the adverse reaction incidence rate in the population studied.

Pediatric

Table 1 Adverse Reactions Reported by 2% or More of Children (Aged 6 to 12 Years) Taking Vyvanse in a 4-Week Clinical Trial

Body System | Preferred Term | Vyvanse (n=218) | Placebo (n=72)
Gastrointestinal Disorders | Abdominal Pain Upper | 12% | 6%
Gastrointestinal Disorders | Vomiting | 9% | 4%
Gastrointestinal Disorders | Nausea | 6% | 3%
Gastrointestinal Disorders | Dry Mouth | 5% | 0%
General Disorder and Administration Site Conditions | Pyrexia | 2% | 1%
Investigations | Weight Decreased | 9% | 1%
Metabolism and Nutrition | Decreased Appetite | 39% | 4%
Nervous System Disorders | Dizziness | 5% | 0%
Nervous System Disorders | Somnolence | 2% | 1%
Psychiatric Disorders | Insomniaa | 23% | 3%
Psychiatric Disorders | Irritability | 10% | 0%
Psychiatric Disorders | Affect lability | 3% | 0%
Psychiatric Disorders | Tic | 2% | 0%
Skin and Subcutaneous Tissue Disorders | Rash | 3% | 0%

a Insomnia includes the following preferred terms reported in the study: Initial Insomnia, Insomnia.

Note: This table includes those reactions for which the incidence in patients taking Vyvanse is at least twice the incidence in patients taking placebo.

Table 2 Adverse Reactions Reported by 2% or More of Adolescent (Aged 13 to 17 Years) Patients Taking Vyvanse in a 4-Week Clinical Trial
Body System | Preferred Term | Vyvanse (n=233) | Placebo (n=77)
Gastrointestinal Disorders | Dry Mouth | 4% | 1%
Investigations | Weight Decreased | 9% | 0%
Metabolism and Nutrition | Decreased Appetite | 34% | 3%
Psychiatric Disorders | Insomniab | 13% | 4%
b Insomnia includes the following preferred terms reported in the study: Initial Insomnia, Insomnia.
Note: This table includes those reactions for which the incidence in patients taking Vyvanse is at least twice the incidence in patients taking placebo.

Adult

Table 3 Adverse Reactions Reported by 2% or More of Adult Patients Taking Vyvanse in a 4-Week Clinical Trial

Body System | Preferred Term | Vyvanse (n=358) | Placebo (n=62)
Gastrointestinal Disorders | Dry Mouth | 26% | 3%
Gastrointestinal Disorders | Diarrhea | 7% | 0%
Gastrointestinal Disorders | Nausea | 7% | 0%
General Disorder and Administration Site Conditions | Feeling Jittery | 4% | 0%
Investigations | Blood Pressure Increased | 3% | 0%
Investigations | Heart Rate Increased | 2% | 0%
Metabolism and Nutrition Disorders | Decreased Appetite | 27% | 3%
Metabolism and Nutrition Disorders | Anorexia | 5% | 0%
Nervous System Disorders | Tremor | 2% | 0%
Psychiatric Disorders | Insomniac | 27% | 8%
Psychiatric Disorders | Anxiety | 6% | 0%
Psychiatric Disorders | Agitation | 3% | 0%
Psychiatric Disorders | Restlessness | 3% | 0%
Respiratory, Thoracic, and Mediastinal Disorders | Dyspnea | 2% | 0%
Skin and Subcutaneous Tissue Disorders | Hyperhidrosis | 3% | 0%

c Insomnia includes the following preferred terms reported in the study: Initial Insomnia, Insomnia, Middle Insomnia.

Note: This table includes those events for which the incidence in patients taking Vyvanse is at least twice the incidence in patients taking placebo.

In addition, adverse reactions observed at a rate of less than 2% included decreased libido and erectile dysfunction.

Vital Signs

Weight Loss - In the controlled adult trial, mean weight loss after 4 weeks of therapy was 2.8 lbs, 3.1 lbs, and 4.3 lbs, for patients receiving final doses of 30 mg, 50 mg, and 70 mg of Vyvanse, respectively, compared to a mean weight gain of 0.5 lbs for patients receiving placebo.

6.2 Postmarketing Reports

The following adverse reactions have been identified during post approval use of Vyvanse. Because these reactions are reported voluntarily from a population of uncertain size, it is not possible to reliably estimate their frequency or establish a causal relationship to drug exposure.

Cardiac Disorders - Palpitation

Eye Disorders - Vision blurred, mydriasis, diplopia

General Disorders and Administration Site Conditions - Fatigue

Hepatobiliary Disorders - Eosinophilic Hepatitis

Immune System Disorders - Anaphylactic reaction, hypersensitivity

Nervous System Disorders - Somnolence, seizure, dyskinesia

Psychiatric Disorder - Psychotic episodes, mania, hallucination, depression, aggression, dysphoria, euphoria, logorrhoea, dermatillomania

Skin and Subcutaneous Tissue Disorder - Stevens-Johnson Syndrome, angioedema, urticaria

6.3 Adverse Reactions Associated with the Use of Amphetamine

Cardiovascular

Palpitations, tachycardia, elevation of blood pressure, sudden death, myocardial infarction. There have been isolated reports of cardiomyopathy associated with chronic amphetamine use.

Central Nervous System

Psychotic episodes at recommended doses, overstimulation, restlessness, dizziness, insomnia, euphoria, dyskinesia, dysphoria, depression, tremor, headache, exacerbation of motor and phonic tics and Tourette's syndrome, seizures, stroke.

Gastrointestinal

Dryness of the mouth, unpleasant taste, diarrhea, constipation, other gastrointestinal disturbances.

Allergic

Urticaria, rashes, and hypersensitivity reactions, including angioedema and anaphylaxis. Serious skin reactions, including Stevens-Johnson Syndrome and Toxic Epidermal Necrolysis have been reported.

Endocrine

Impotence, changes in libido.

7 DRUG INTERACTIONS

7.1 Agents Whose Blood Levels May be Impacted by Vyvanse

Extended release guanfacine: In a drug interaction study (N=40), administration of an extended release guanfacine (4 mg) in combination with Vyvanse (50 mg) increased guanfacine maximum plasma concentration by 19%, whereas, exposure (area under the curve; AUC) was increased by 7%. These small changes are not expected to be clinically meaningful. In this study, no effect on d-amphetamine exposure was observed following co-administration of extended release guanfacine and Vyvanse.

7.2 Agents that Lower Blood Levels of Amphetamines

Urinary Acidifying Agents

These agents (ammonium chloride, sodium acid phosphate, etc.) increase the concentration of the ionized species of the amphetamine molecule, thereby increasing urinary excretion.

Methenamine Therapy

Urinary excretion of amphetamines is increased, and efficacy is reduced, by acidifying agents used in methenamine therapy.

7.3 Agents that Increase Blood Levels of Amphetamines

Urinary Alkalinizing Agents

These agents (acetazolamide, some thiazides) increase the concentration of the non-ionized species of the amphetamine molecule, thereby decreasing urinary excretion.

Monoamine Oxidase Inhibitors

MAOI antidepressants, as well as a metabolite of furazolidone, slow amphetamine metabolism. This slowing potentiates amphetamines, increasing their effect on the release of norepinephrine and other monoamines from adrenergic nerve endings; this can cause headaches and other signs of hypertensive crisis. A variety of toxic neurological effects and malignant hyperpyrexia can occur, sometimes with fatal results.

7.4 Agents Whose Effects May be Reduced by Amphetamines

Adrenergic Blockers

Adrenergic blockers are inhibited by amphetamines.

Antihistamines

Amphetamines may counteract the sedative effect of antihistamines.

Antihypertensives

Amphetamines may antagonize the hypotensive effects of antihypertensives.

Veratrum Alkaloids

Amphetamines inhibit the hypotensive effect of veratrum alkaloids.

Ethosuximide

Amphetamines may delay intestinal absorption of ethosuximide.

7.5 Agents Whose Effects May be Potentiated by Amphetamines

Antidepressants, Tricyclic

Amphetamines may enhance the activity of tricyclic antidepressants or sympathomimetic agents; d-amphetamine with desipramine or protriptyline and possibly other tricyclics cause striking and sustained increases in the concentration of d-amphetamine in the brain; cardiovascular effects can be potentiated.

Meperidine

Amphetamines potentiate the analgesic effect of meperidine.

Phenobarbital

Amphetamines may delay intestinal absorption of phenobarbital; co-administration of phenobarbital may produce a synergistic anticonvulsant action.

Phenytoin

Amphetamines may delay intestinal absorption of phenytoin; co-administration of phenytoin may produce a synergistic anticonvulsant action.

7.6 Agents that May Reduce the Effects of Amphetamines

Chlorpromazine

Chlorpromazine blocks dopamine and norepinephrine receptors, thus inhibiting the central stimulant effects of amphetamines, and can be used to treat amphetamine poisoning.

Haloperidol

Haloperidol blocks dopamine receptors, thus inhibiting the central stimulant effects of amphetamines.

Lithium Carbonate

The anorectic and stimulatory effects of amphetamines may be inhibited by lithium carbonate.

7.7 Agents that May Potentiate the Effects of Amphetamines

Norepinephrine

Amphetamines enhance the adrenergic effect of norepinephrine.

Propoxyphene Overdosage

In cases of propoxyphene overdosage, amphetamine CNS stimulation is potentiated and fatal convulsions can occur.

7.8 Drug/Laboratory Test Interactions

Amphetamines can cause a significant elevation in plasma corticosteroid levels. This increase is greatest in the evening. Amphetamine may interfere with urinary steroid determinations.

8 USE IN SPECIFIC POPULATIONS

8.1 Pregnancy

Animal reproduction studies of lisdexamfetamine dimesylate have not been performed. Studies have been performed with the active metabolite of lisdexamfetamine, d-amphetamine, either alone or in combination with l-amphetamine, as noted below.

Teratogenic Effects

Pregnancy Category C

Amphetamine (d- to l-enantiomer ratio of 3:1) had no apparent effects on embryofetal morphological development or survival when orally administered to pregnant rats and rabbits throughout the period of organogenesis at doses of up to 6 and 16 mg/kg/day, respectively. Fetal malformations and death have been reported in mice following parenteral administration of d-amphetamine doses of 50 mg/kg/day or greater to pregnant animals. Administration of these doses was also associated with severe maternal toxicity.

A number of studies in rodents indicate that prenatal or early postnatal exposure to amphetamine (d- or d,l-) at doses similar to those used clinically can result in longterm neurochemical and behavioral alterations. Reported behavioral effects include learning and memory deficits, altered locomotor activity, and changes in sexual function.

There are no adequate and well-controlled studies in pregnant women. There has been one report of severe congenital bony deformity, tracheo-esophageal fistula, and anal atresia (vater association) in a baby born to a woman who took dextroamphetamine sulfate with lovastatin during the first trimester of pregnancy. Amphetamines should be used during pregnancy only if the potential benefit justifies the potential risk to the fetus.

Nonteratogenic Effects

Infants born to mothers dependent on amphetamines have an increased risk of premature delivery and low birth weight. Also, these infants may experience symptoms of withdrawal as demonstrated by dysphoria, including agitation, and significant lassitude.

8.2 Labor and Delivery

The effects of Vyvanse on labor and delivery in humans is unknown.

8.3 Nursing Mothers

Amphetamines are excreted into human milk. Mothers taking amphetamines should be advised to refrain from nursing.

8.4 Pediatric Use

Vyvanse is indicated for use in pediatric patients with ADHD aged 6 to 17 years. Vyvanse has not been studied in children under 6 years of age. Long-term effects of amphetamines in children have not been well established.

A study was conducted in which juvenile rats received oral doses of 4, 10, or 40 mg/kg/day of lisdexamfetamine dimesylate from day 7 to day 63 of age. These doses are approximately 0.3, 0.7, and 3 times the maximum recommended human daily dose of 70 mg on a mg/m^2 basis. Dose-related decreases in food consumption, bodyweight gain, and crown-rump length were seen; after a four-week drug-free recovery period, bodyweights and crown-rump lengths had significantly recovered in females but were still substantially reduced in males. Time to vaginal opening was delayed in females at the highest dose, but there were no drug effects on fertility when the animals were mated beginning on day 85 of age.

In a study in which juvenile dogs received lisdexamfetamine dimesylate for 6 months beginning at 10 weeks of age, decreased bodyweight gain was seen at all doses tested (2, 5, and 12 mg/kg/day, which are approximately 0.5, 1, and 3 times the maximum recommended human daily dose on a mg/m^2 basis). This effect partially or fully reversed during a four-week drug-free recovery period.

8.5 Geriatric Use

Vyvanse has not been studied in the geriatric population.

9 DRUG ABUSE AND DEPENDENCE

9.1 Controlled Substance

Vyvanse is classified as a Schedule II controlled substance.

9.2 Abuse and Dependence

Amphetamines have been extensively abused. Tolerance, extreme psychological dependence, and severe social disability have occurred. There are reports of patients who have increased the dosage to levels many times higher than recommended. Abrupt cessation following prolonged high-dosage administration results in extreme fatigue and mental depression; changes are also noted on the sleep EEG. Manifestations of chronic intoxication with amphetamines may include severe dermatoses, marked insomnia, irritability, hyperactivity, and personality changes. The most severe manifestation of chronic intoxication is psychosis, often clinically indistinguishable from schizophrenia.

Human Studies

In a human abuse liability study, when equivalent oral doses of 100 mg lisdexamfetamine dimesylate and 40 mg immediate-release d-amphetamine sulfate were administered to individuals with a history of drug abuse, lisdexamfetamine dimesylate 100 mg produced subjective responses on a scale of "Drug Liking Effects" (primary endpoint) that were significantly less than d-amphetamine immediate-release 40 mg. However, oral administration of 150 mg lisdexamfetamine dimesylate produced increases in positive subjective responses on this scale that were statistically indistinguishable from the positive subjective responses produced by 40 mg of oral immediate-release d-amphetamine and 200 mg of diethylpropion (C-IV).^1

Intravenous administration of 50 mg lisdexamfetamine dimesylate to individuals with a history of drug abuse produced positive subjective responses on scales measuring "Drug Liking", "Euphoria", "Amphetamine Effects", and "Benzedrine Effects" that were greater than placebo but less than those produced by an equivalent dose (20 mg) of intravenous d-amphetamine.

Animal Studies

In animal studies, lisdexamfetamine dimesylate produced behavioral effects qualitatively similar to those of the CNS stimulant d-amphetamine. In monkeys trained to self-administer cocaine, intravenous lisdexamfetamine dimesylate maintained self-administration at a rate that was statistically less than that for cocaine, but greater than that of placebo.

10 OVERDOSAGE

Individual patient response to amphetamines varies widely. Toxic symptoms may occur idiosyncratically at low doses.

Symptoms: Manifestations of acute overdosage with amphetamines include restlessness, tremor, hyperreflexia, rapid respiration, confusion, assaultiveness, hallucinations, panic states, hyperpyrexia, and rhabdomyolysis. Fatigue and depression usually follow the central nervous system stimulation. Cardiovascular effects include arrhythmias, hypertension or hypotension, and circulatory collapse. Gastrointestinal symptoms include nausea, vomiting, diarrhea, and abdominal cramps. Fatal poisoning is usually preceded by convulsions and coma.

Treatment: Consult with a Certified Poison Control Center for up-to-date guidance and advice. Management of acute amphetamine intoxication is largely symptomatic and includes gastric lavage, administration of activated charcoal, administration of a cathartic, and sedation. Experience with hemodialysis or peritoneal dialysis is inadequate to permit recommendation in this regard. Acidification of the urine increases amphetamine excretion but is believed to increase risk of acute renal failure if myoglobinuria is present. If acute severe hypertension complicates amphetamine overdosage, administration of intravenous phentolamine has been suggested. However, a gradual drop in blood pressure will usually result when sufficient sedation has been achieved. Chlorpromazine antagonizes the central stimulant effects of amphetamines and can be used to treat amphetamine intoxication.

The prolonged release of Vyvanse in the body should be considered when treating patients with overdose.

11 DESCRIPTION

Vyvanse (lisdexamfetamine dimesylate) is designed as a capsule for once-a-day oral administration. The chemical designation for lisdexamfetamine dimesylate is (2S)-2,6-diamino-N-[(1S)-1-methyl-2-phenylethyl] hexanamide dimethanesulfonate. The molecular formula is C15H25N3O•(CH4O3S)2, which corresponds to a molecular weight of 455.60. The chemical structure is:

Lisdexamfetamine dimesylate is a white to off-white powder that is soluble in water (792 mg/mL). Vyvanse capsules contain 20 mg, 30 mg, 40 mg, 50 mg, 60 mg, and 70 mg of lisdexamfetamine dimesylate and the following inactive ingredients: microcrystalline cellulose, croscarmellose sodium, and magnesium stearate. The capsule shells (imprinted with NRP104) contain gelatin, titanium dioxide, and one or more of the following: D&C Red #28, D&C Yellow #10, FD&C Blue #1, FD&C Green #3, and FD&C Red #40. The capsule shells (imprinted with S489) contain gelatin, titanium dioxide, and one or more of the following: FD&C Red #3, FD&C Yellow #6, FD&C Blue #1, Black Iron Oxide, and Yellow Iron Oxide.

12 CLINICAL PHARMACOLOGY

12.1 Mechanism of Action

Lisdexamfetamine is a prodrug of dextroamphetamine. After oral administration, lisdexamfetamine is rapidly absorbed from the gastrointestinal tract and converted primarily in blood due to the hydrolytic activity of red blood cells to dextroamphetamine, which is responsible for the drug's activity. Amphetamines are non-catecholamine sympathomimetic amines with CNS stimulant activity. The mode of therapeutic action in Attention Deficit Hyperactivity Disorder (ADHD) is not known. Amphetamines are thought to block the reuptake of norepinephrine and dopamine into the presynaptic neuron and increase the release of these monoamines into the extraneuronal space. The parent drug, lisdexamfetamine, does not bind to the sites responsible for the reuptake of norepinephrine and dopamine in vitro.

12.3 Pharmacokinetics

Pharmacokinetic studies of dextroamphetamine after oral administration of lisdexamfetamine have been conducted in healthy adult and pediatric (aged 6 to 12) patients with ADHD.

In 18 pediatric patients (aged 6 to 12) with ADHD, the Tmax of dextroamphetamine was approximately 3.5 hours following single-dose oral administration of lisdexamfetamine dimesylate either 30 mg, 50 mg, or 70 mg after an 8-hour overnight fast. The Tmax of lisdexamfetamine was approximately 1 hour. Linear pharmacokinetics of dextroamphetamine after single-dose oral administration of lisdexamfetamine dimesylate was established over the dose range of 30 mg to 70 mg in children aged 6 to 12 years.

There is no unexpected accumulation of dextroamphetamine AUC at steady state in healthy adults and no accumulation of lisdexamfetamine after once-daily dosing for 7 consecutive days.

Food does not affect the observed AUC and Cmax of dextroamphetamine in healthy adults after single-dose oral administration of 70 mg of Vyvanse capsules but prolongs Tmax by approximately 1 hour (from 3.8 hrs at fasted state to 4.7 hrs after a high fat meal). After an 8-hour fast, the AUCs for dextroamphetamine following oral administration of lisdexamfetamine dimesylate in solution and as intact capsules were equivalent.

Weight/Dose normalized AUC and Cmax were 22% and 12% lower, respectively, in adult females than in males on day 7 following a 70 mg/day dose of lisdexamfetamine dimesylate for 7 days. Weight/Dose normalized AUC and Cmax values were the same in girls and boys following single doses of 30-70 mg.

Metabolism and Excretion

After oral administration, lisdexamfetamine is rapidly absorbed from the gastrointestinal tract. Lisdexamfetamine is converted to dextroamphetamine and l-lysine primarily in blood due to the hydrolytic activity of red blood cells. In vitro data demonstrated that red blood cells have a high capacity for metabolism of lisdexamfetamine; substantial hydrolysis occurred even at low hematocrit levels (33% of normal). Lisdexamfetamine is not metabolized by cytochrome P450 enzymes. Following the oral administration of a 70 mg dose of radiolabeled lisdexamfetamine dimesylate to 6 healthy subjects, approximately 96% of the oral dose radioactivity was recovered in the urine and only 0.3% recovered in the feces over a period of 120 hours. Of the radioactivity recovered in the urine, 42% of the dose was related to amphetamine, 25% to hippuric acid, and 2% to intact lisdexamfetamine. Plasma concentrations of unconverted lisdexamfetamine are low and transient, generally becoming non-quantifiable by 8 hours after administration. The plasma elimination half-life of lisdexamfetamine typically averaged less than one hour in studies of lisdexamfetamine dimesylate in volunteers.

Dextroamphetamine is known to inhibit monoamine oxidase. The ability of dextroamphetamine and its metabolites to inhibit various P450 isozymes and other enzymes has not been adequately elucidated. In vitro experiments with human microsomes indicate minor inhibition of CYP2D6 by amphetamine and minor inhibition of CYP1A2, 2D6, and 3A4 by one or more metabolites, but there are no in vivo studies of p450 enzyme inhibition.

Special Populations

Age

The pharmacokinetics of dextroamphetamine is similar in pediatric (aged 6 to 12) and adolescent (aged 13 to 17) ADHD patients, and healthy adult volunteers. Any differences in kinetics seen after oral administration are a result of differences in mg/kg dosing.

Gender

Systemic exposure to dextroamphetamine is similar for men and women given the same mg/kg dose.

Race

Formal pharmacokinetic studies for race have not been conducted.

13 NONCLINICAL TOXICOLOGY

13.1 Carcinogenesis/ Mutagenesis and Impairment of Fertility

Carcinogenicity studies of lisdexamfetamine dimesylate have not been performed.

No evidence of carcinogenicity was found in studies in which d-, l-amphetamine (enantiomer ratio of 1:1) was administered to mice and rats in the diet for 2 years at doses of up to 30 mg/kg/day in male mice, 19 mg/kg/day in female mice, and 5 mg/kg/day in male and female rats.

Lisdexamfetamine dimesylate was not clastogenic in the mouse bone marrow micronucleus test in vivo and was negative when tested in the E. coli and S. typhimurium components of the Ames test and in the L5178Y/TK^+- mouse lymphoma assay in vitro.

Amphetamine (d- to l-enantiomer ratio of 3:1) did not adversely affect fertility or early embryonic development in the rat at doses of up to 20 mg/kg/day.

13.2 Animal Toxicology

Acute administration of high doses of amphetamine (d- or d,l-) has been shown to produce long-lasting neurotoxic effects, including irreversible nerve fiber damage, in rodents. The significance of these findings to humans is unknown.

14 CLINICAL STUDIES

The efficacy of Vyvanse in the treatment of ADHD was established on the basis of two controlled trials in children aged 6 to 12 years, one controlled trial in adolescents aged 13 to 17 years, and two controlled trials in adults who met Diagnostic and Statistical Manual of Mental Disorders, 4th edition (DSM-IV-TR) criteria for ADHD [see INDICATIONS AND USAGE (1)].

Pediatric

A double-blind, randomized, placebo-controlled, parallel-group study was conducted in children aged 6 to 12 (N=290) who met DSM-IV criteria for ADHD (either the combined type or the hyperactive-impulsive type). Patients were randomized to receive final doses of 30 mg, 50 mg, or 70 mg of Vyvanse or placebo once daily in the morning for a total of four weeks of treatment. All subjects receiving Vyvanse were initiated on 30 mg for the first week of treatment. Subjects assigned to the 50 mg and 70 mg dose groups were titrated by 20 mg per week until they achieved their assigned dose. The primary efficacy outcome was change in Total Score from baseline to endpoint in investigator ratings on the ADHD Rating Scale (ADHD-RS), a measure of the core symptoms of ADHD. Endpoint was defined as the last post-randomization treatment week (i.e. Weeks 1 through 4) for which a valid score was obtained. All Vyvanse dose groups were superior to placebo in the primary efficacy outcome. Mean effects at all doses were fairly similar, although the highest dose (70 mg/day) was numerically superior to both lower doses (30 mg/day and 50 mg/day). The effects were maintained throughout the day based on parent ratings (Conners' Parent Rating Scale) in the morning (approximately 10 am), afternoon (approximately 2 pm), and early evening (approximately 6 pm).

A double-blind, placebo-controlled, randomized, crossover design, analog classroom study was conducted in children aged 6 to 12 (N=52) who met DSM-IV criteria for ADHD (either the combined type or the hyperactive-impulsive type). Following a 3-week open-label dose titration with Adderall XR®, patients were randomly assigned to continue the same dose of Adderall XR (10 mg, 20 mg, or 30 mg), Vyvanse (30 mg, 50 mg, or 70 mg), or placebo once daily in the morning for 1 week each treatment. A significant difference in patient behavior, based upon the average of investigator ratings on the Swanson, Kotkin, Agler, M.Flynn, and Pelham (SKAMP)-Deportment scores across 7 assessments conducted at 2, 3, 4.5, 6, 8, 10, and 12 hours post-dose were observed between patients who received Vyvanse compared to patients who received placebo. The drug effect was similar for all 7 sessions.

A second double-blind, placebo-controlled, randomized, crossover design, analog classroom study was conducted in children aged 6 to 12 (N=129) who met DSM-IV criteria for ADHD (either the combined type or the hyperactive-impulsive type). Following a 4-week open-label dose titration with Vyvanse (30 mg, 50 mg, 70 mg), patients were randomly assigned to continue Vyvanse or placebo once daily in the morning for 1 week each treatment. A significant difference in patient behavior, based upon the average of investigator ratings on the SKAMP-Deportment scores across all 7 assessments conducted at 1.5, 2.5, 5.0, 7.5, 10.0, 12.0, and 13.0 hours post-dose, were observed between patients who received Vyvanse compared to patients who received placebo.

A double-blind, randomized, placebo-controlled, parallel-group study was conducted in adolescents aged 13 to 17 (N=314) who met DSM-IV criteria for ADHD. In this study, patients were randomized in a 1:1:1:1 ratio to a daily morning dose of Vyvanse (30 mg/day, 50 mg/day or 70 mg/day) or placebo for a total of four weeks of treatment. All subjects receiving Vyvanse were initiated on 30 mg for the first week of treatment. Subjects assigned to the 50 mg and 70 mg dose groups were titrated by 20 mg per week until they achieved their assigned dose. The primary efficacy outcome was change in Total Score from baseline to endpoint in investigator ratings on the ADHD Rating Scale (ADHD-RS), a measure of the core symptoms of ADHD. Endpoint was defined as the last post-randomization treatment week (i.e. Weeks 1 through 4) for which a valid score was obtained. All Vyvanse dose groups were superior to placebo in the primary efficacy outcome.

Adult

A double-blind, randomized, placebo-controlled, parallel-group study was conducted in adults (N=420) who met DSM-IV criteria for ADHD. In this study, patients were randomized to receive final doses of 30 mg, 50 mg, or 70 mg of Vyvanse or placebo for a total of four weeks of treatment. All subjects receiving Vyvanse were initiated on 30 mg for the first week of treatment. Subjects assigned to the 50 mg and 70 mg dose groups were titrated by 20 mg per week until they achieved their assigned dose. The primary efficacy outcome was change in Total Score from baseline to endpoint in investigator ratings on the ADHD Rating Scale (ADHD-RS), a measure of the core symptoms of ADHD. Endpoint was defined as the last post-randomization treatment week (i.e. Weeks 1 through 4) for which a valid score was obtained. All Vyvanse dose groups were superior to placebo in the primary efficacy outcome.

The second study was a multi-center, randomized, double-blind, placebo-controlled, crossover design, modified analog classroom study of Vyvanse to simulate a workplace environment in 142 adults who met DSM-IV-TR criteria for ADHD. There was a 4-week open-label, dose optimization phase with Vyvanse (30 mg/day, 50 mg/day, or 70 mg/day in the morning). Subjects were then randomized to one of two treatment sequences: 1) Vyvanse (optimized dose) followed by placebo, each for one week, or 2) placebo followed by Vyvanse, each for one week. Efficacy assessments occurred at the end of each week, using the Permanent Product Measure of Performance (PERMP). The PERMP is a skill-adjusted math test that measures attention in ADHD. Vyvanse treatment, compared to placebo, resulted in a statistically significant improvement in attention across all post-dose time points, as measured by average PERMP total scores over the course of one assessment day, as well as at each time point measured. The PERMP assessments were administered at pre-dose (-0.5 hours) and at 2, 4, 8, 10, 12, and 14 hours post-dose.

15 REFERENCES

^1 Jasinski DR, Krishnan S. Abuse liability and safety of oral lisdexamfetamine dimesylate in individuals with a history of stimulant abuse. Journal of Psychopharmacology. 2009; 23(4);419-27.

16 HOW SUPPLIED/STORAGE AND HANDLING

Vyvanse capsules 30 mg: white body/orange cap (imprinted with NRP104 or S489 and 30 mg),

Bottles of 10 | NDC 54868-5916-0
Bottles of 30 | NDC 54868-5916-1

Vyvanse capsules 40 mg: white body/blue green cap (imprinted with NRP104 or S489 and 40 mg),

Bottles of 10 | NDC 54868-6009-0
Bottles of 30 | NDC 54868-6009-1

Vyvanse capsules 50 mg: white body/blue cap (imprinted with NRP104 or S489 and 50 mg),

Bottles of 10 | NDC 54868-5827-0
Bottles of 30 | NDC 54868-5827-1

Vyvanse capsules 70 mg: blue body/orange cap (imprinted with NRP104 or S489 and 70 mg),

Bottles of 10 | NDC 54868-3655-0
Bottles of 30 | NDC 54868-3655-1

Dispense in a tight, light-resistant container as defined in the USP.

Store at 25° C (77° F). Excursions permitted to 15-30° C (59-86° F) [see USP Controlled Room Temperature]

17 PATIENT COUNSELING INFORMATION

See Medication Guide

17.1 Information on Medication Guide

Prescribers or other health professionals should inform patients, their families, and their caregivers about the benefits and risks associated with treatment with Vyvanse and should counsel them in its appropriate use. A patient Medication Guide is available for Vyvanse. The prescriber or health professional should instruct patients, their families, and their caregivers to read the Medication Guide and should assist them in understanding its contents. Patients should be given the opportunity to discuss the contents of the Medication Guide and to obtain answers to any questions they may have. The complete text of the Medication Guide is attached to the package insert.

17.2 Controlled Substance Status/Potential for Abuse, Misuse, and Dependence

Patients should be advised that Vyvanse is a federally controlled substance because it can be abused or lead to dependence. Additionally, it should be emphasized that Vyvanse should be stored in a safe place to prevent misuse and/or abuse. Patient history (including family history) of abuse or dependence on alcohol, prescription medicines, or illicit drugs should be evaluated [see Drug Abuse and Dependence (9)].

17.3 Serious Cardiovascular Risks

Patients should be advised of serious cardiovascular risk (including sudden death, myocardial infarction, stroke, and hypertension) with Vyvanse. Patients who develop symptoms such as exertional chest pain, unexplained syncope, or other symptoms suggestive of cardiac disease during treatment should undergo a prompt cardiac evaluation [see Warnings and Precautions (5.1)].

17.4 Psychiatric Risks

Prior to initiating treatment with a stimulant, patients with comorbid depressive symptoms should be adequately screened to determine if they are at risk for bipolar disorder. Such screening should include a detailed psychiatric history, including a family history of suicide, bipolar disorder, and/or depression. Additionally, stimulant therapy at usual doses may cause treatment-emergent psychotic or manic symptoms in patients without prior history of psychotic symptoms or mania [see Warnings and Precautions (5.2)].

17.5 Growth

Growth should be monitored during treatment with stimulants, and patients who are not growing or gaining weight as expected may need to have their treatment interrupted. [see Warnings and Precautions (5.6)].

17.6 Pregnancy

Patients should be advised to notify their physicians if they become pregnant or intend to become pregnant during treatment [see Dosage and Administration (2) and Use in Specific Populations (8.1)].

17.7 Nursing

Patients should be advised not to breast feed if they are taking Vyvanse [see USE IN SPECIFIC POPULATIONS (8.3)].

17.8 Impairment in Ability to Operate Machinery or Vehicles

Amphetamines may impair the ability of the patient to engage in potentially hazardous activities such as operating machinery or vehicles; the patient should therefore be cautioned accordingly.

Pharmacist: Medication Guide to be dispensed to patients

Manufactured for: Shire US Inc., Wayne, PA 19087

Made in USA

For more information call 1-800-828-2088

Vyvanse® is a trademark of Shire LLC

©2011 Shire US Inc.

US Pat No. 7,105,486 and US Pat No. 7,223,735

Last Modified: 08/2011

Relabeling and Repackaging by:
Physicians Total Care, Inc.
Tulsa, Oklahoma 74146

MEDICATION GUIDE

VYVANSE®

(lisdexamfetamine dimesylate) CII

Read the Medication Guide that comes with Vyvanse before you or your child starts taking it and each time you get a refill. There may be new information. This Medication Guide does not take the place of talking to your doctor about you or your child's treatment with Vyvanse.

What is the most important information I should know about Vyvanse?
Vyvanse is a stimulant medicine. The following have been reported with use of stimulant medicines.
1. Heart-related problems:
• sudden death in patients who have heart problems or heart defects
• stroke and heart attack in adults
• increased blood pressure and heart rate
Tell your doctor if you or your child have any heart problems, heart defects, high blood pressure, or a family history of these problems.
Your doctor should check you or your child carefully for heart problems before starting Vyvanse.
Your doctor should check your or your child's blood pressure and heart rate regularly during treatment with Vyvanse.
Call your doctor right away if you or your child has any signs of heart problems such as chest pain, shortness of breath, or fainting while taking Vyvanse.
2. Mental (Psychiatric) problems:
All Patients
• new or worse behavior and thought problems
• new or worse bipolar illness
• new or worse aggressive behavior or hostility
Children and Teenagers
• new psychotic symptoms (such as hearing voices, believing things that are not true, are suspicious) or new manic symptoms
Tell your doctor about any mental problems you or your child have, or about a family history of suicide, bipolar illness, or depression.
Call your doctor right away if you or your child have any new or worsening mental symptoms or problems while taking Vyvanse, especially seeing or hearing things that are not real, believing things that are not real, or are suspicious.

What Is Vyvanse?

Vyvanse is a central nervous system stimulant prescription medicine. It is used for the treatment of Attention-Deficit Hyperactivity Disorder (ADHD). Vyvanse may help increase attention and decrease impulsiveness and hyperactivity in patients with ADHD.

Vyvanse should be used as a part of a total treatment program for ADHD that may include counseling or other therapies.

Vyvanse is a federally controlled substance (CII) because it can be abused or lead to dependence. Keep Vyvanse in a safe place to prevent misuse and abuse. Selling or giving away Vyvanse may harm others, and is against the law.
Tell your doctor if you or your child have (or have a family history of) ever abused or been dependent on alcohol, prescription medicines or street drugs.

Who should not take Vyvanse?

Vyvanse should not be taken if you or your child:

- have heart disease or hardening of the arteries
- have moderate to severe high blood pressure
- have hyperthyroidism
- have an eye problem called glaucoma
- are very anxious, tense, or agitated
- have a history of drug abuse
- are taking or have taken within the past 14 days an anti-depression medicine called a monoamine oxidase inhibitor or MAOI.
- is sensitive to, allergic to, or had a reaction to other stimulant medicines

Vyvanse has not been studied in children less than 6 years old.

Vyvanse may not be right for you or your child. Before starting Vyvanse tell your or your child's doctor about all health conditions (or a family history of) including:

- heart problems, heart defects, high blood pressure
- mental problems including psychosis, mania, bipolar illness, or depression
- tics or Tourette's syndrome
- liver or kidney problems
- thyroid problems
- seizures or have had an abnormal brain wave test (EEG)

Tell your doctor if you or your child is pregnant, planning to become pregnant, or breastfeeding.

Can Vyvanse be taken with other medicines?

Tell your doctor about all of the medicines that you or your child take including prescription and non-prescription medicines, vitamins, and herbal supplements. Vyvanse and some medicines may interact with each other and cause serious side effects. Sometimes the doses of other medicines will need to be adjusted while taking Vyvanse.

Your doctor will decide whether Vyvanse can be taken with other medicines.

Especially tell your doctor if you or your child takes:

- anti-depression medicines including MAOIs
- anti-psychotic medicines
- lithium
- blood pressure medicines
- seizure medicines
- narcotic pain medicines

Know the medicines that you or your child takes. Keep a list of your medicines with you to show your doctor and pharmacist.

Do not start any new medicine while taking Vyvanse without talking to your doctor first.

How should Vyvanse be taken?

- Take Vyvanse exactly as prescribed. Vyvanse comes in 6 different strength capsules. Your doctor may adjust the dose until it is right for you or your child.
- Take Vyvanse once a day in the morning.
- Vyvanse can be taken with or without food.
- From time to time, your doctor may stop Vyvanse treatment for a while to check ADHD symptoms.
- Your doctor may do regular checks of the blood, heart, and blood pressure while taking Vyvanse. Children should have their height and weight checked often while taking Vyvanse. Vyvanse treatment may be stopped if a problem is found during these check-ups.
- If you or your child takes too much Vyvanse or overdoses, call your doctor or poison control center right away, or get emergency treatment.

What are possible side effects of Vyvanse?

See "What is the most important information I should know about Vyvanse?" for information on reported heart and mental problems.

Other serious side effects include:

- slowing of growth (height and weight) in children
- seizures, mainly in patients with a history of seizures
- eyesight changes or blurred vision

Common side effects include:

- upper belly pain
- dizziness
- irritability
- nausea
- weight loss
- decreased appetite
- dry mouth
- trouble sleeping
- vomiting

Vyvanse may affect your or your child's ability to drive or do other dangerous activities.

Talk to your doctor if you or your child has side effects that are bothersome or do not go away.

This is not a complete list of possible side effects. Ask your doctor or pharmacist for more information.

Call your doctor for medical advice about side effects. You may report side effects to FDA at 1-800-FDA-1088.

How should I store Vyvanse?

- Store Vyvanse in a safe place at room temperature, 59 to 86° F (15 to 30° C). Protect from light.
- Keep Vyvanse and all medicines out of the reach of children.

General information about Vyvanse

Medicines are sometimes prescribed for purposes other than those listed in a Medication Guide. Do not use Vyvanse for a condition for which it was not prescribed. Do not give Vyvanse to other people, even if they have the same condition. It may harm them and it is against the law.

This Medication Guide summarizes the most important information about Vyvanse. If you would like more information, talk with your doctor. You can ask your doctor or pharmacist for information about Vyvanse that was written for healthcare professionals. For more information about Vyvanse, please contact Shire US Inc. at 1-800-828-2088.

What are the ingredients in Vyvanse?

Active Ingredient: lisdexamfetamine dimesylate

Inactive Ingredients: microcrystalline cellulose, croscarmellose sodium, and magnesium stearate. The capsule shells (imprinted with NRP104) contain gelatin, titanium dioxide, and one or more of the following: D&C Red #28, D&C Yellow #10, FD&C Blue #1, FD&C Green #3, and FD&C Red #40. The capsule shells (imprinted with S489) contain gelatin, titanium dioxide, and one or more of the following: FD&C Red #3, FD&C Yellow #6, FD&C Blue #1, Black Iron Oxide, Yellow Iron Oxide.

This Medication Guide has been approved by the U.S. Food and Drug Administration.

©2011 Shire US Inc.

US Pat No. 7,105,486 and US Pat No. 7,223,735

Last Modified: 08/2011

PACKAGE LABEL

VYVANSE®

(lisdexamfetamine dimesylate) CII

30 mg Capsules

40 mg Capsules

50 mg Capsules

70 mg Capsules